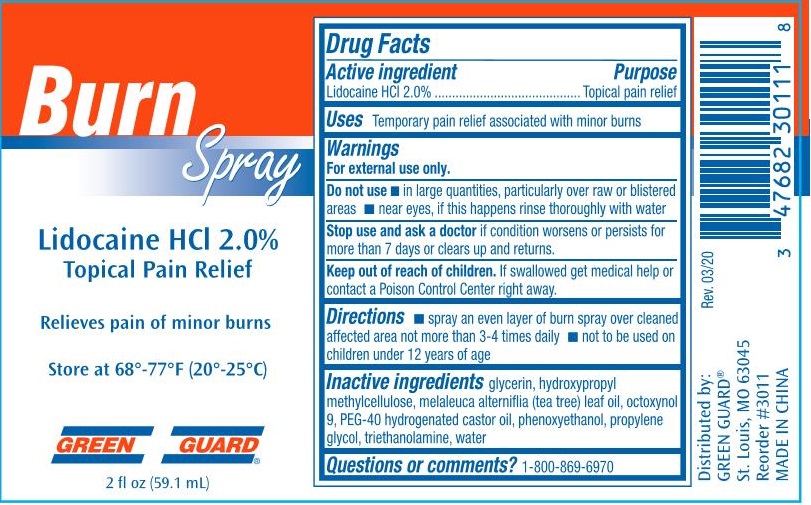 DRUG LABEL: Green Guard  Burn
NDC: 47682-330 | Form: SPRAY
Manufacturer: Unifirst First Aid Corporation
Category: otc | Type: HUMAN OTC DRUG LABEL
Date: 20250908

ACTIVE INGREDIENTS: LIDOCAINE HYDROCHLORIDE 20 g/1 L
INACTIVE INGREDIENTS: WATER; HYPROMELLOSES; TROLAMINE; PHENOXYETHANOL; GLYCERIN; TEA TREE OIL; PEG-40 CASTOR OIL; OCTOXYNOL 9; PROPYLENE GLYCOL

Green Guard First Aid & Safety Burn Spray

Active ingredient

Lidocaine HCl 2.0%

Purpose

Topical pain relief

Uses

Temporary pain relief associated with minor burns

Warnings

For external use only.

Do not use

- in large quantities, particularly over raw or blisterd areas
- near eyes, if this happens rinse thoroughly with water

Stop use and ask a doctor if condition worsens or persists for more than 7 days or clears up and returns.

Keep out of reach of children. If swallowed get medical help or contact a Poison Control Center right away.

Directions

- spray an even layer of burn spray over cleaned affected area not more than 3-4 times daily
- not to be used on children under 12 years of age

Inactive ingredients

glycerin, hdroxypropyl methylcellulose, melaleuca alterniflia (tea tree) leaf oil, octoxynol 9, PEG-40 hydrogenated castor oil, phenoxyethanol, propylene glycol, triethanolamine, water

Questions or comments? 1-800-869-6970

PACKAGE LABEL

Burn Spray

Lidocaine HCl 2.0%

TopicalPain Relief

Relieves pain of minor burns

Store at 68°-77°F (20°-25°C)

Green Guard®

2 fl oz (59.1 mL)